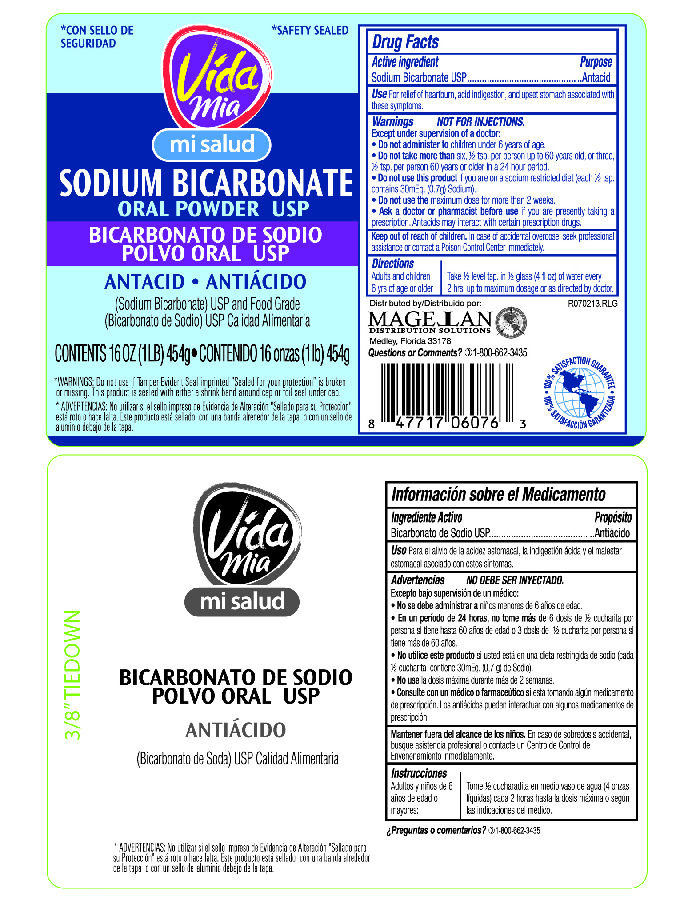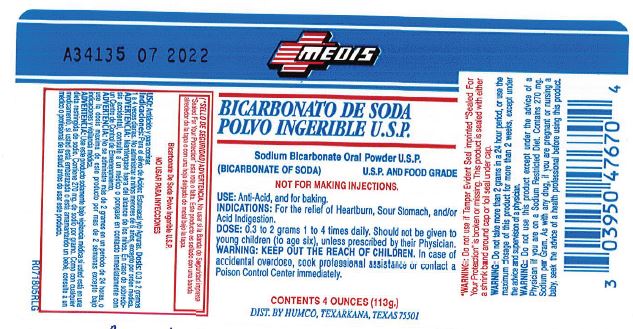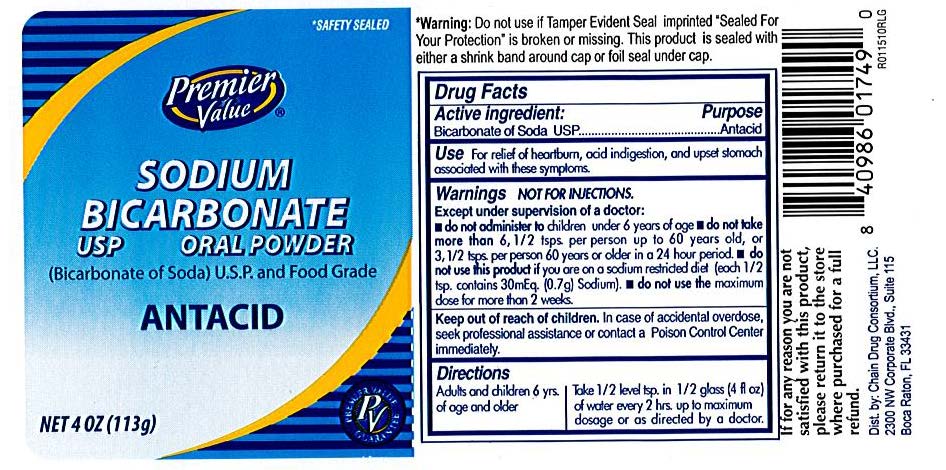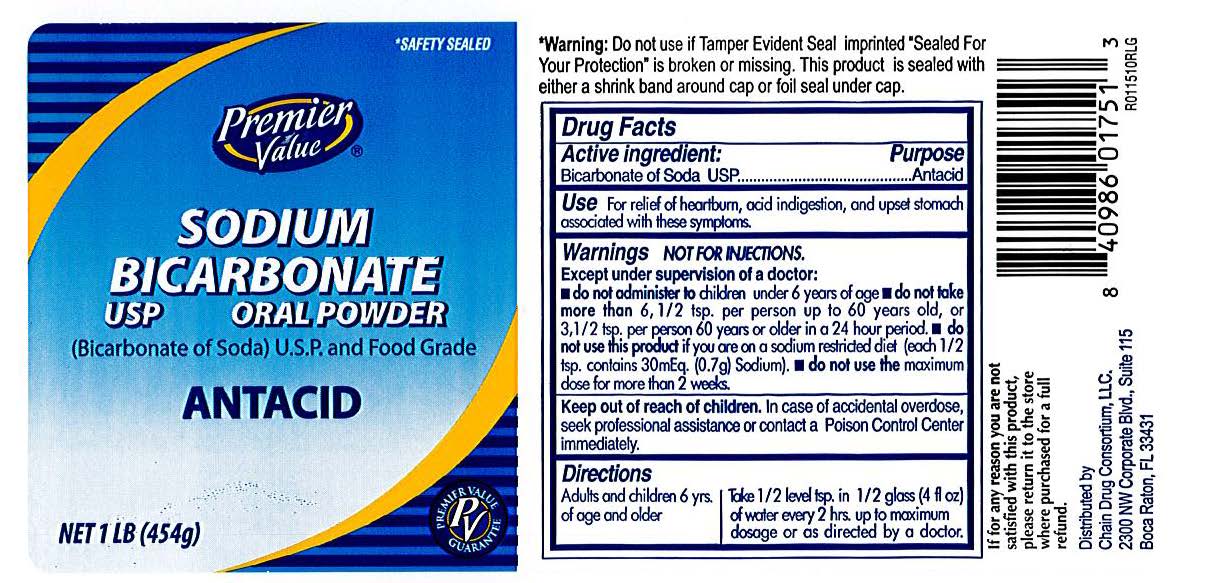 DRUG LABEL: Sodium Bicarbonate
NDC: 82645-904 | Form: POWDER
Manufacturer: Pharma Nobis, LLC
Category: otc | Type: HUMAN OTC DRUG LABEL
Date: 20231222

ACTIVE INGREDIENTS: SODIUM BICARBONATE 1000 mg/1 g
INACTIVE INGREDIENTS: WATER

Private Label Sodium Bicarbonate

Drug Facts

Active Ingredient

Soduim Bicarbonate, USP

Purpose

Antacid

Use

For relief of heartburn, acid indigestion, and upset stomach associated with these symptoms.

Warnings NOT FOR INJECTIONS

Except under supervision of a doctor do not administer to children under 6 years of age.

Do not take more than six, 1/2 tsp. per person up to 60 years old, or three 1/2 tsp. per person 60 years or older in a 24 hour period.

Do not use this product if you are on a sodium restricted diet (each 1/2 tsp. contains 30 mEq (0.7 g) Sodium).

Do not use the maximum does more than 2 weeks.

Ask a doctor or pharmacist before use if

you are currently taking a prescription drug. Antacids may interact with certain prescription drugs.

Keep out of reach of children.

In case of accidental overdose, seek professional assistance or contact a Poison Control Center immediately.

Directions

Adult and children 6 yrs of age and older:

Take 1/2 tsp. in 1/2 g;ass (4 fl oz) of water every 2 hrs. up to maximum dosage or as directed by doctor.

Inactive ingredients

none

Premier Value Label

4 oz

16 oz